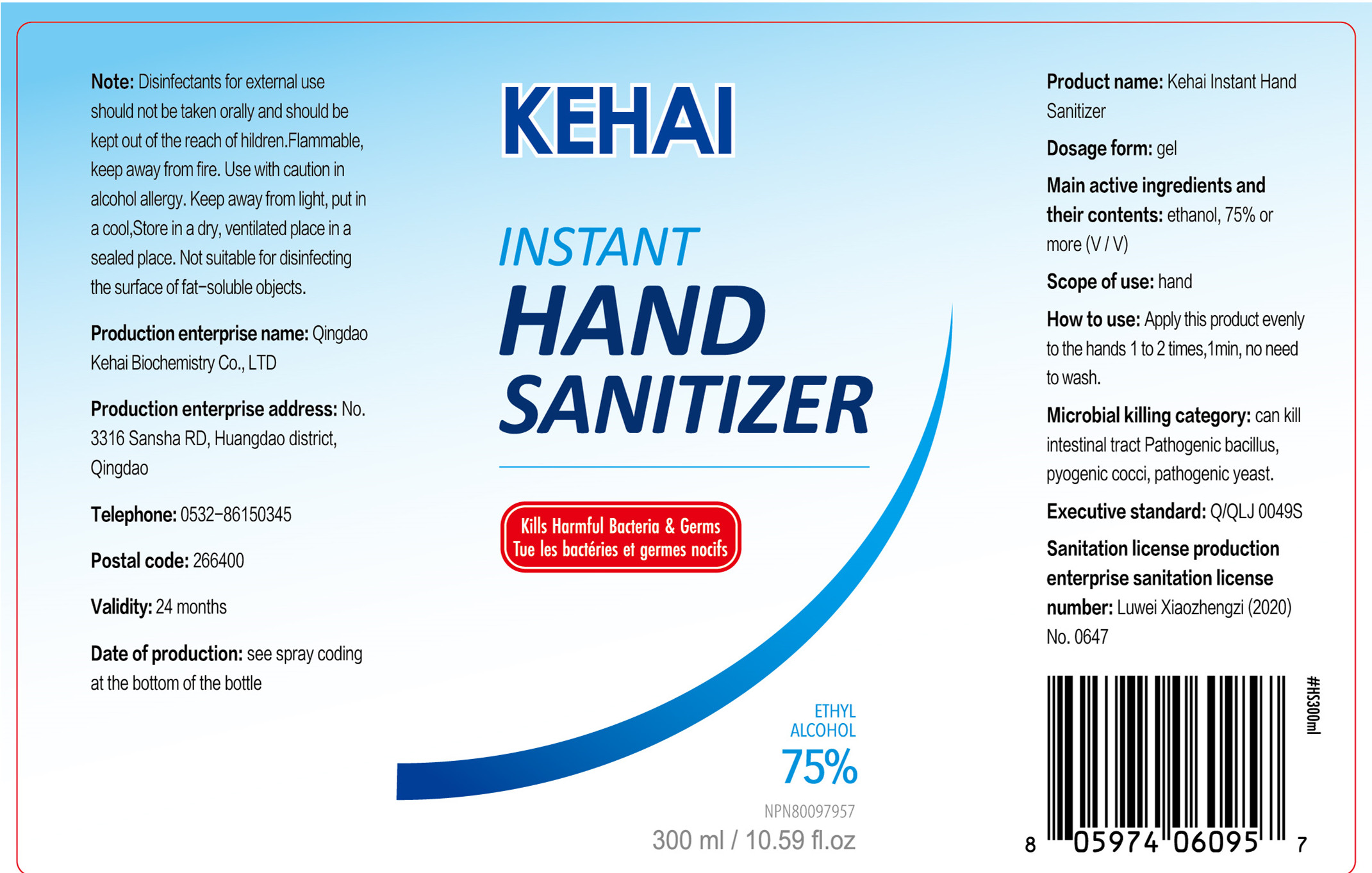 DRUG LABEL: Kehai Instant Hand Sanitizer
NDC: 52697-001 | Form: GEL
Manufacturer: Qingdao Kehai Biochemistry Co., LTD
Category: otc | Type: HUMAN OTC DRUG LABEL
Date: 20200622

ACTIVE INGREDIENTS: ALCOHOL 225 mL/300 mL
INACTIVE INGREDIENTS: WATER; GLYCERIN; CARBOMER HOMOPOLYMER, UNSPECIFIED TYPE; AMINOMETHYLPROPANOL

DOSAGE AND ADMINISTRATION

Put in a cool,Store in a dry, ventilated place in a sealed place.

INACTIVE INGREDIENT

Aqua/Water,Glycerin,Carbomer,Aminomethyl Propanol

INDICATIONS AND USAGE

Apply this product evenly to the hands 1 to2 times,1min, no need to wash.

ACTIVE INGREDIENT

Alcohol

keep out of reach of children

PURPOSE

Disinfection
Sterilization
No Rinseing

WARNINGS

Disinfectants for extermaluse should not be taken orally and should be kept out of the reach of hildren.Flammable,keep away from fire. Use with caution inalcohol alergy Keep away from light, put in a cool,Store in a dry, ventilated place ina sealed place. Not suitable for disinfecting the surface of fat-soluble objects.